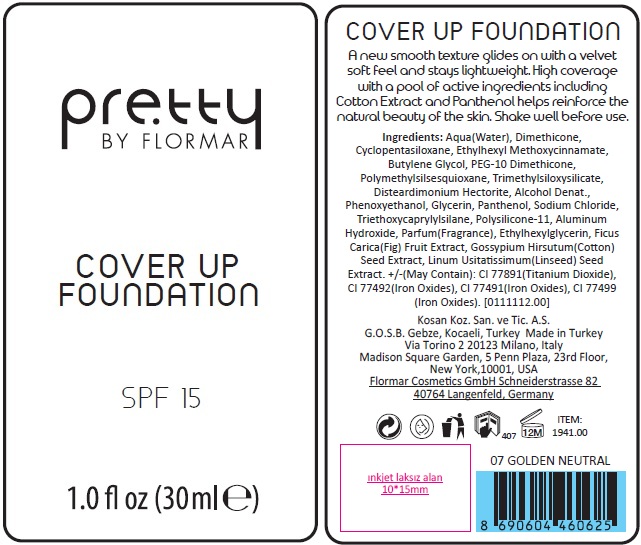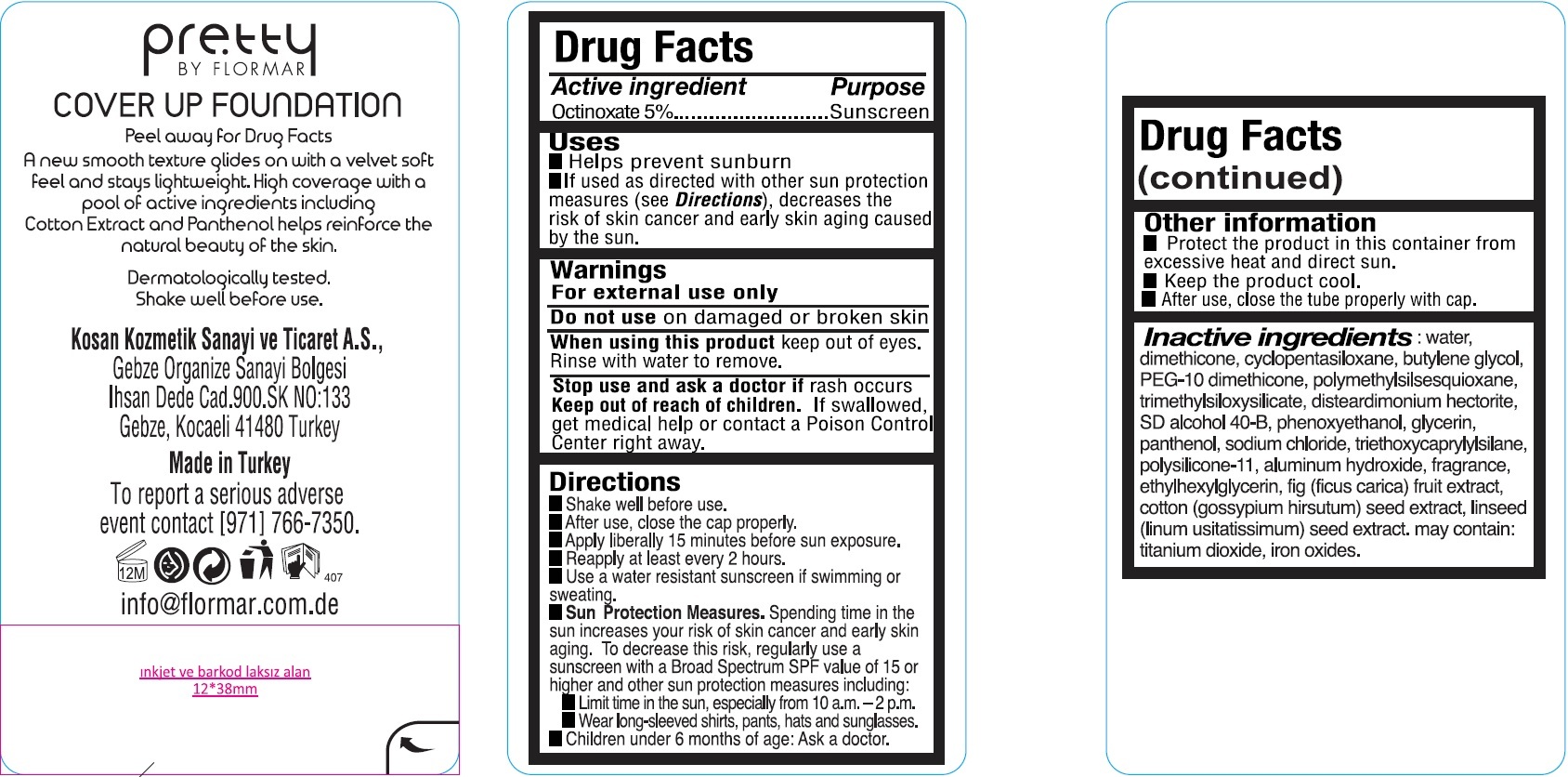 DRUG LABEL: Pretty by Flormar Cover up Foundation 007 Neutral
NDC: 61722-311 | Form: CREAM
Manufacturer: Kosan Kozmetik Sanayi ve Ticaret A.S.
Category: otc | Type: HUMAN OTC DRUG LABEL
Date: 20200128

ACTIVE INGREDIENTS: OCTINOXATE 50 mg/1 mL
INACTIVE INGREDIENTS: WATER; CYCLOMETHICONE 5; BUTYLENE GLYCOL; DIMETHICONE/VINYL DIMETHICONE CROSSPOLYMER (SOFT PARTICLE); DIMETHICONE; PEG-10 DIMETHICONE (600 CST); DISTEARDIMONIUM HECTORITE; POLYMETHYLSILSESQUIOXANE (4.5 MICRONS); PHENOXYETHANOL; GLYCERIN; SODIUM CHLORIDE; ETHYLHEXYLGLYCERIN; .ALPHA.-TOCOPHEROL ACETATE; TRIETHOXYCAPRYLYLSILANE; ALUMINUM HYDROXIDE; LAURETH-12; COTTON SEED; FLAX SEED; CAPRYLYL GLYCOL; .ALPHA.-HEXYLCINNAMALDEHYDE; BENZYL SALICYLATE; BUTYLPHENYL METHYLPROPIONAL; ISOMETHYL-.ALPHA.-IONONE; LINALOOL, (+/-)-

Pretty by Flormar Cover up Foundation 007 Neutral

Active ingredient

Octinoxate 5%

Purpose

Sunscreen

Uses

- Helps prevent sunburn
- If used as directed with other sun protection measures (see Directions), decreases the risk of skin cancer and early skin aging caused by the sun.

Warnings

For external use only

Do not use

on damaged or broken skin

When using this product

keep out of eyes. Rinse with water to remove.

Stop use and ask a doctor if

rash occurs

Keep out of reach of children.

If swallowed, get medical help or contact a Poison Control Center right away.

Directions

- Shake well before use.
- After use, close the cap properly.
- Apply liberally 15 minutes before sun exposure.
- Reapply at least every 2 hours.
- Use a water resistant sunscreen if swimming or sweating.
- Sun Protection Measures. Spending time in the sun increases your risk of skin cancer and early skin aging. To decrease this risk, regularly use a sunscreen with a Broad Spectrum SPF value of 15 or higher and other sun protection measures including:
- Limit time in the sun, especially from 10 a.m. -2 p.m.
- Wear long-sleeved shirts, pants, hats and sunglasses.
- Children under 6 months of age: Ask a doctor.

Other information

- Protect the product in this container from excessive heat and direct sun.
- Keep the product cool.
- After use, close the tube properly with cap.

Inactive ingredients:

water, cyclopentasiloxane, butylene glycol, polysilicone-11, cetyl PEG/PPG-10/1 dimethicone, dimethicone, PEG-10 dimethicone, trimethylsiloxysilicate, disteardimonium hectorite, SD alcohol 40-B, polymethylsilsesquioxane, phenoxyethanol, methyl methacrylate
crosspolymer, glycerin, sodium chloride, fragrance, ethylhexylglycerin, tocopheryl acetate, triethoxycaprylylsilane, aluminum hydroxide,
laureth-12, fig (ficus carica) fruit extract, cotton (gossypium hirsutum) seed extract, linseed (linum usitatissimum) seed extract, caprylyl glycol, hexyl cinnamal, benzyl salicylate, butylphenyl methylpropional, alpha-isomethyl ionone, linalool. may contain: titanium dioxide, iron oxides.